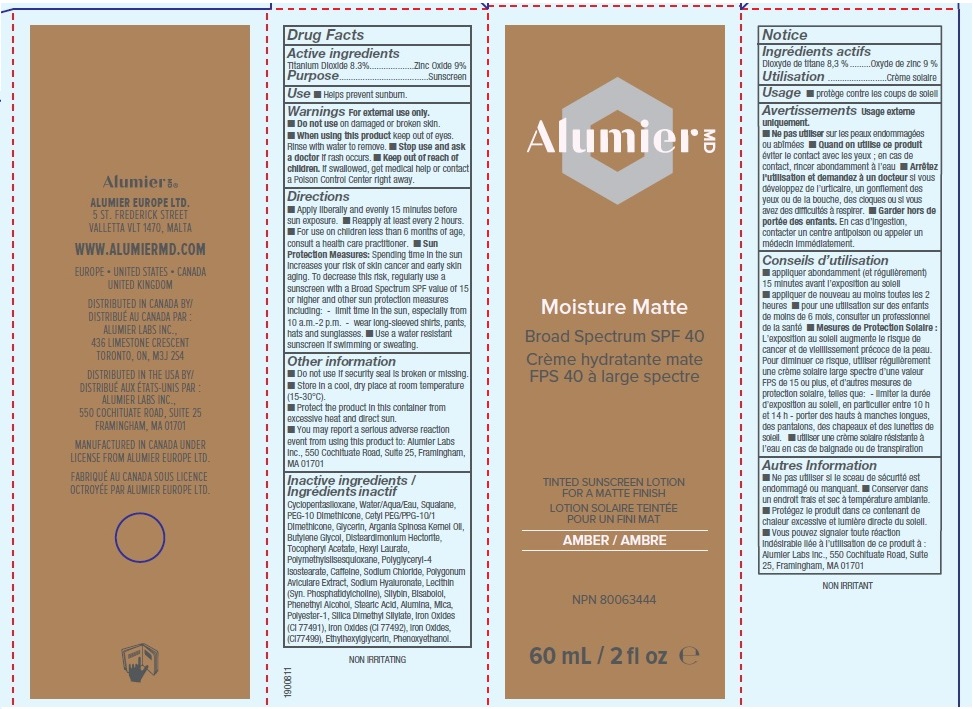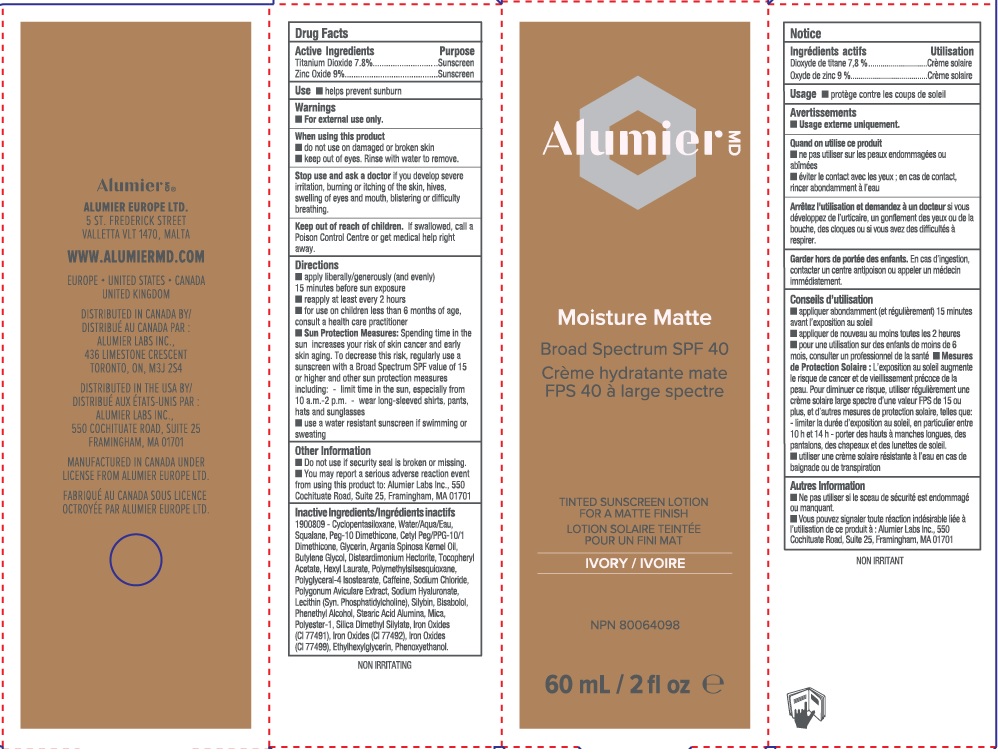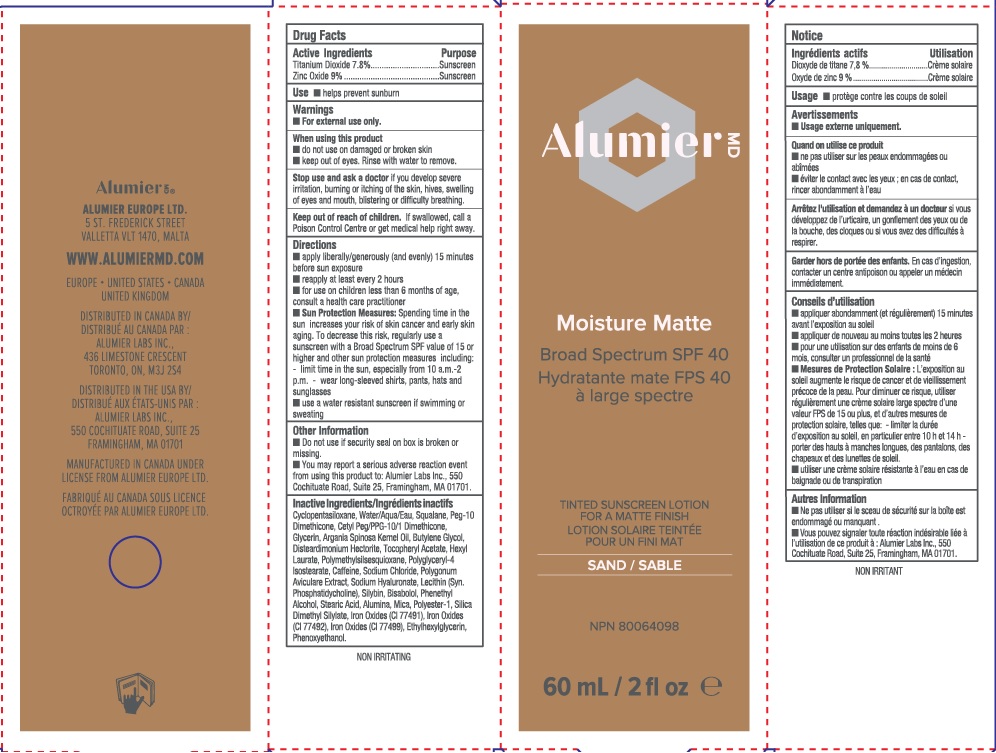 DRUG LABEL: Alumier MD Moisture Matte Broad Spectrum SPF 40 Sunscreen Amber
NDC: 69473-014 | Form: LOTION
Manufacturer: Alumier Labs
Category: otc | Type: HUMAN OTC DRUG LABEL
Date: 20241203

ACTIVE INGREDIENTS: ZINC OXIDE 90 mg/1 mL; TITANIUM DIOXIDE 83 mg/1 mL
INACTIVE INGREDIENTS: WATER; SQUALANE; DISTEARDIMONIUM HECTORITE; .ALPHA.-TOCOPHEROL ACETATE; HEXYL LAURATE; POLYGLYCERYL-4 ISOSTEARATE; POLYGONUM AVICULARE TOP; PEG-10 DIMETHICONE (600 CST); ARGAN OIL; FERRIC OXIDE YELLOW; FERROSOFERRIC OXIDE; CYCLOMETHICONE 5; GLYCERIN; BUTYLENE GLYCOL; POLYMETHYLSILSESQUIOXANE (4.5 MICRONS); LECITHIN, SOYBEAN; PHENYLETHYL ALCOHOL; STEARIC ACID; SILICA DIMETHYL SILYLATE; SODIUM CHLORIDE; HYALURONATE SODIUM; SILIBININ; LEVOMENOL; PHENOXYETHANOL; CAFFEINE; CETYL PEG/PPG-10/1 DIMETHICONE (HLB 2); ALUMINUM OXIDE; MICA; FERRIC OXIDE RED; ETHYLHEXYLGLYCERIN

Alumier MD Moisture Matte Broad Spectrum SPF 40 Sunscreen

Active ingredients

Amber Shade:

Titanium Dioxide 8.3%

Zinc Oxide 9%

Ivory and Sand Shades:

Titanium Dioxide 7.8%

Zinc Oxide 9%

Purpose

Sunscreen

Use

- Helps prevent sunburn.

Warnings

For external use only.

When using this product

- do not use on damaged or broken skin
- keep out of eyes. Rinse with water to remove.

Stop use and ask a doctor

if you develop severe irritation, burning or itching of the skin, hives, swelling of eyes and mouth, blistering or difficulty breathing.

Keep out of reach of children.

If swallowed, call a Poison Control Center or get medical help right away.

Directions

- Apply liberally/generously (and evenly) 15 minutes before sun exposure.
- Reapply at least every 2 hours.
- For use on children less than 6 months of age, consult a health care practitioner.
- Sun Protection Measures: Spending time in the sun increases your risk of skin cancer and early skin aging. To decrease this risk, regularly use a sunscreen with a Broad Spectrum SPF value of 15 or higher and other sun protection measures including:
- limit time in the sun, especially from 10 a.m.-2 p.m.
- wear long-sleeved shirts, pants, hats and sunglasses.
- use a water resistant sunscreen if swimming or sweating.

Other information

- Do not use if security seal is broken or missing.
- You may report a serious adverse reaction event from using this product to: Alumier Labs Inc., 550 Cochituate Road, Suite 25, Framingham MA 01701

Inactive ingredients

Cyclopentasiloxane, Water/Aqua/Eau, Squalane, PEG-10 Dimethicone, Cetyl PEG/PPG-10/1 Dimethicone, Glycerin, Argania Spinosa Kernel Oil, Butylene Glycol, Disteardimonium Hectorite, Tocopheryl Acetate, Hexyl Laurate, Polymethylsilsesquioxane, Polyglyceryl-4 Isostearate, Caffeine, Sodium Chloride, Polygonum Aviculare Extract, Sodium Hyaluronate, Lecithin (Syn. Phosphatidylcholine), Silybin, Bisabolol, Phenethyl Alcohol, Stearic Acid, Alumina, Mica, Polyester-1, Silica Dimethyl Silylate, Iron Oxides (CI 77491), Iron Oxides (CI 77492), Iron Oxides (CI 77499), Ethylhexylglycerin, Phenoxyethanol.

Company Information

Distributed in the USA by Alumier Labs Inc.,

550 Cochituate Road, Suite 25

Framingham, MA 01701